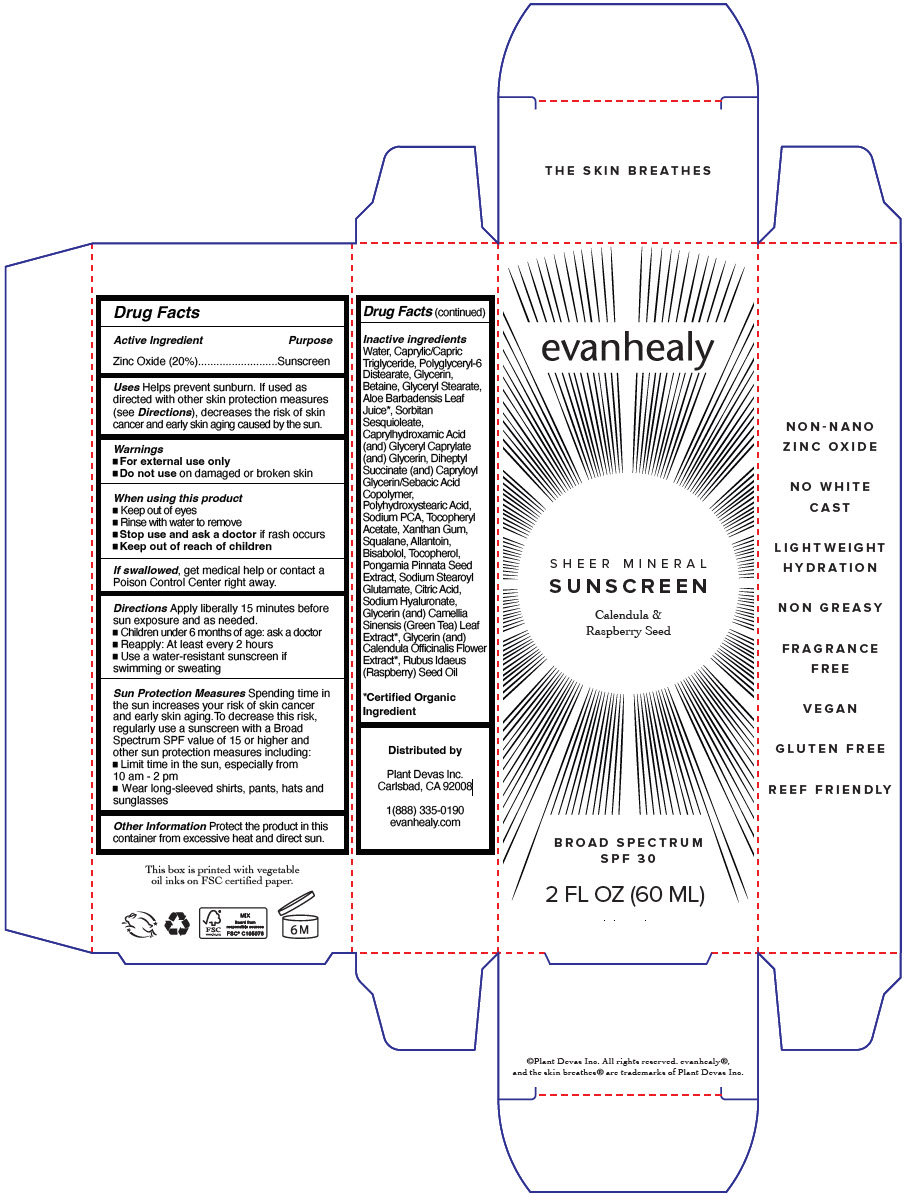 DRUG LABEL: SHEER MINERAL SUNSCREEN
NDC: 84009-816 | Form: CREAM
Manufacturer: Plant Devas Inc. dba evanhealy
Category: otc | Type: HUMAN OTC DRUG LABEL
Date: 20250402

ACTIVE INGREDIENTS: Zinc Oxide 20 g/100 mL
INACTIVE INGREDIENTS: Water; Medium-Chain Triglycerides; Polyglyceryl-6 Distearate; Glycerin; Betaine; Glyceryl Monostearate; Aloe Vera Leaf; Sorbitan Sesquioleate; Caprylhydroxamic Acid; Glyceryl Monocaprylate; Diheptyl Succinate; Sodium Pyrrolidone Carboxylate; .Alpha.-Tocopherol Acetate; Xanthan Gum; Squalane; Allantoin; Levomenol; Tocopherol; Pongamia Pinnata Seed; Sodium Stearoyl Glutamate; Citric Acid Monohydrate; Hyaluronate Sodium; Green Tea Leaf; Calendula Officinalis Flower; Raspberry Seed Oil

SHEER MINERAL SUNSCREEN

Drug Facts

Active Ingredient

Zinc Oxide (20%)

Purpose

Sunscreen

Uses

Helps prevent sunburn. If used as directed with other skin protection measures (see Directions), decreases the risk of skin cancer and early skin aging caused by the sun.

Warnings

- For external use only
- Do not use on damaged or broken skin

When using this product

- Keep out of eyes
- Rinse with water to remove
- Stop use and ask a doctor if rash occurs

- Keep out of reach of children

If swallowed, get medical help or contact a Poison Control Center right away.

Directions

Apply liberally 15 minutes before sun exposure and as needed.

- Children under 6 months of age: ask a doctor
- Reapply: At least every 2 hours
- Use a water-resistant sunscreen if swimming or sweating

Sun Protection Measures

Spending time in the sun increases your risk of skin cancer and early skin aging.To decrease this risk, regularly use a sunscreen with a Broad Spectrum SPF value of 15 or higher and other sun protection measures including:

- Limit time in the sun, especially from 10 am - 2 pm
- Wear long-sleeved shirts, pants, hats and sunglasses

Other Information

Protect the product in this container from excessive heat and direct sun.

Inactive ingredients

Water, Caprylic/Capric Triglyceride, Polyglyceryl-6 Distearate, Glycerin, Betaine, Glyceryl Stearate, Aloe Barbadensis Leaf Juice [Certified Organic Ingredient] , Sorbitan Sesquioleate, Caprylhydroxamic Acid (and) Glyceryl Caprylate (and) Glycerin, Diheptyl Succinate (and) Capryloyl Glycerin/Sebacic Acid Copolymer, Polyhydroxystearic Acid, Sodium PCA, Tocopheryl Acetate, Xanthan Gum, Squalane, Allantoin, Bisabolol, Tocopherol, Pongamia Pinnata Seed Extract, Sodium Stearoyl Glutamate, Citric Acid, Sodium Hyaluronate, Glycerin (and) Camellia Sinensis (Green Tea) Leaf Extract, Glycerin (and) Calendula Officinalis Flower Extract, Rubus Idaeus (Raspberry) Seed Oil

Distributed by

Plant Devas Inc.
Carlsbad, CA 92008

PRINCIPAL DISPLAY PANEL - 60 ML Tube Box

evanhealy

SHEER MINERAL
SUNSCREEN

Calendula &
Raspberry Seed

BROAD SPECTRUM
SPF 30

2 FL OZ (60 ML)